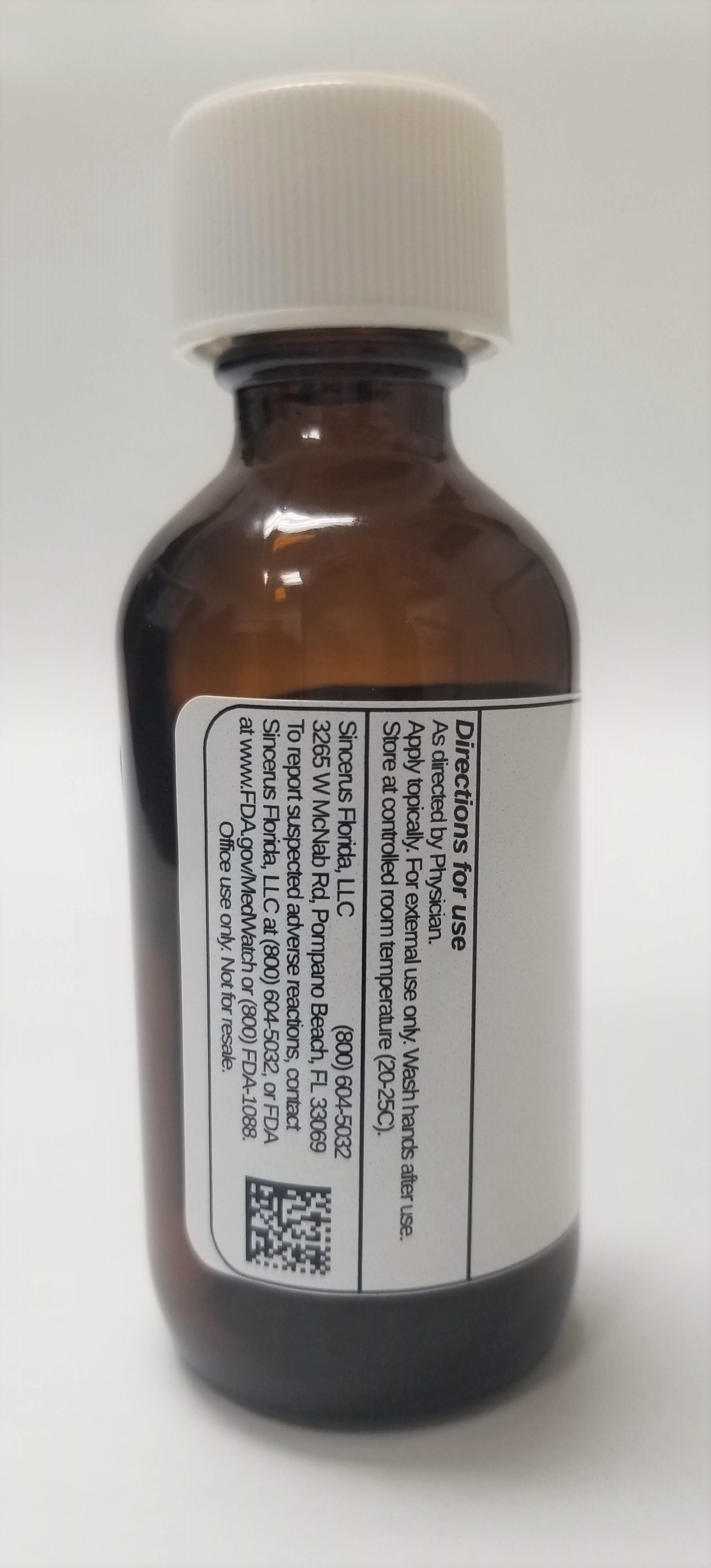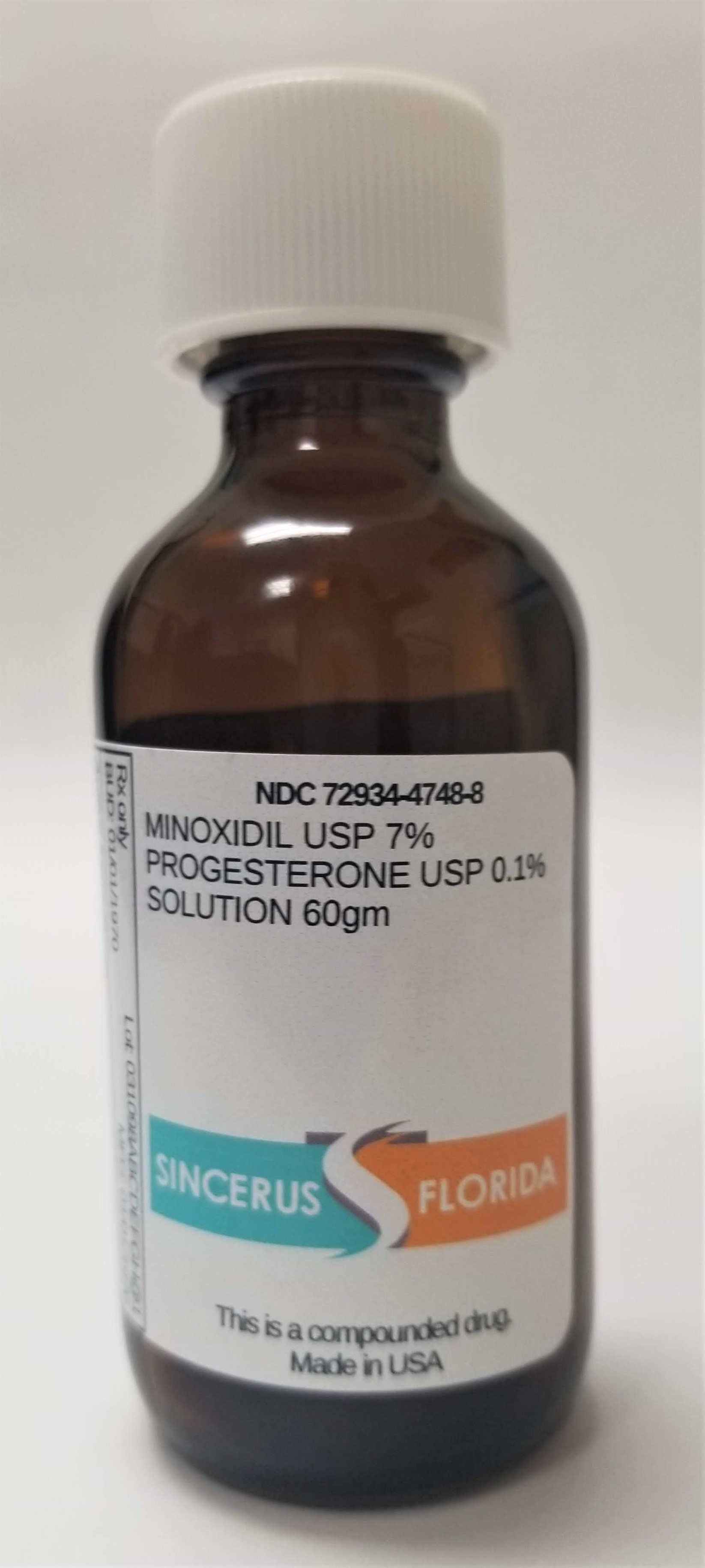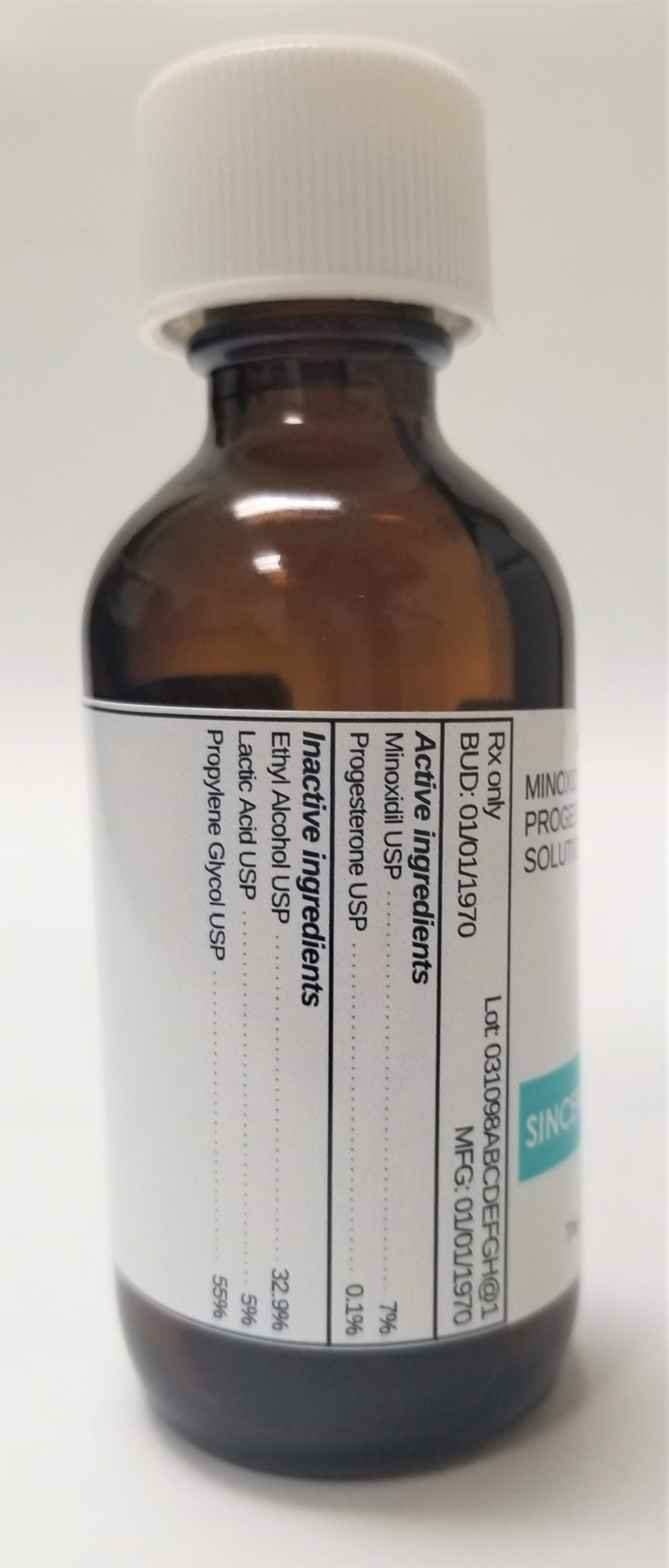 DRUG LABEL: MINOXIDIL 7% / PROGESTERONE 0.1%
NDC: 72934-4748 | Form: SOLUTION
Manufacturer: Sincerus Florida, LLC
Category: prescription | Type: HUMAN PRESCRIPTION DRUG LABEL
Date: 20190424

ACTIVE INGREDIENTS: MINOXIDIL 7 g/100 g; PROGESTERONE 0.1 g/100 g

MINOXIDIL 7% / PROGESTERONE 0.1%